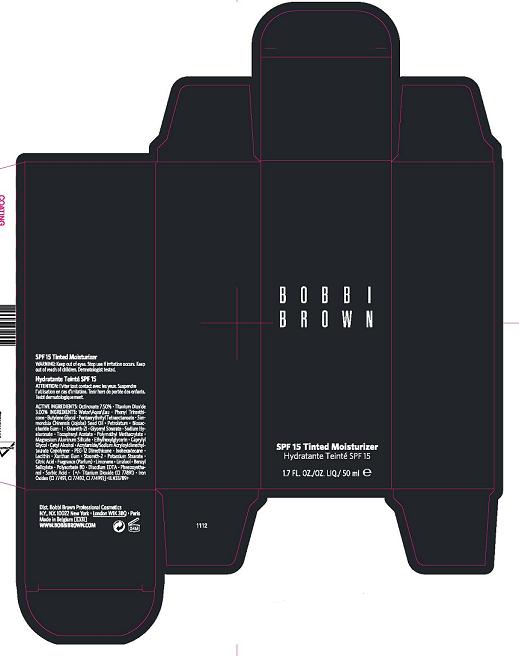 DRUG LABEL: TINTED MOISTURIZER
NDC: 64141-743 | Form: LIQUID
Manufacturer: Bobbi Brown Professional Cosmetics Inc.
Category: otc | Type: HUMAN OTC DRUG LABEL
Date: 20100430

ACTIVE INGREDIENTS: OCTINOXATE  7.5 mL/100 mL; TITANIUM DIOXIDE 3.0 mL/100 mL

ACTIVE INGREDIENT

ACTIVE INGREDIENTS: OCTINOXATE 7.50% [] TITANIUM DIOXIDE 3.00%

WARNINGS

WARNING: KEEP OUT OF EYES. STOP USE IF IRRITATION OCCURS. KEEP OUT OF REACH OF CHILDREN.

PACKAGE LABEL

PRINCIPAL DISPLAY PANEL:

BOBBI BROWN

SPF 15 TINTED MOISTURIZER

1.7 FL OZ/OZ LIQ/50 ML

BOBBI BROWN PROFESSIONAL COSMETICS
NY NY 10022